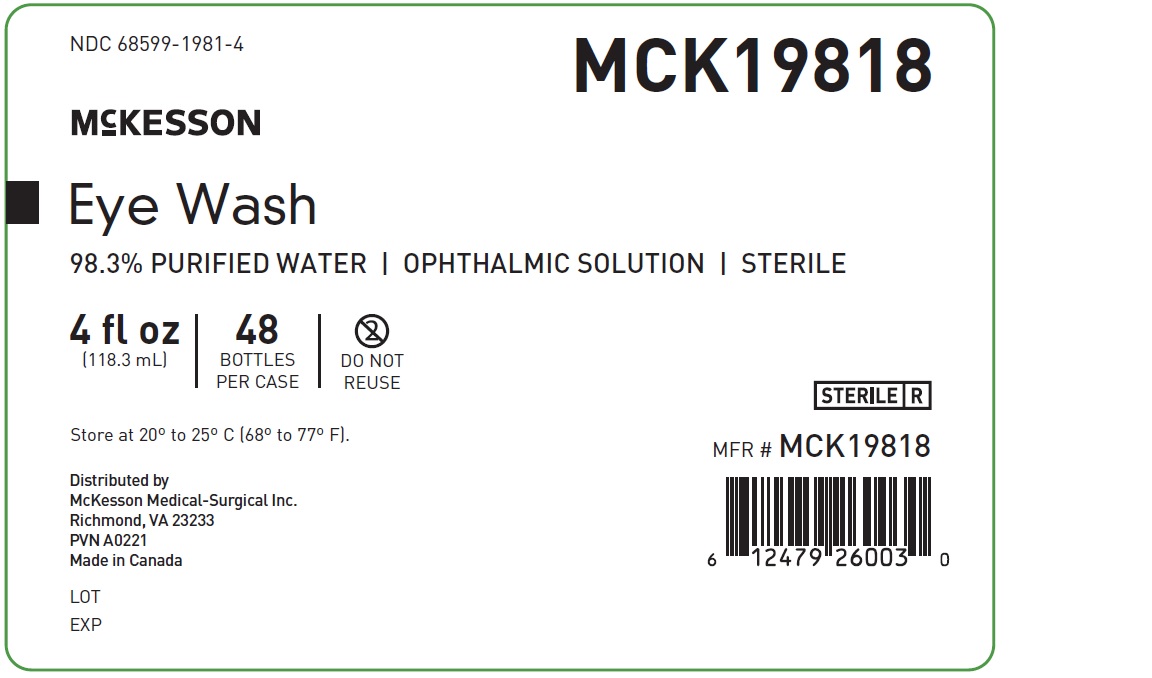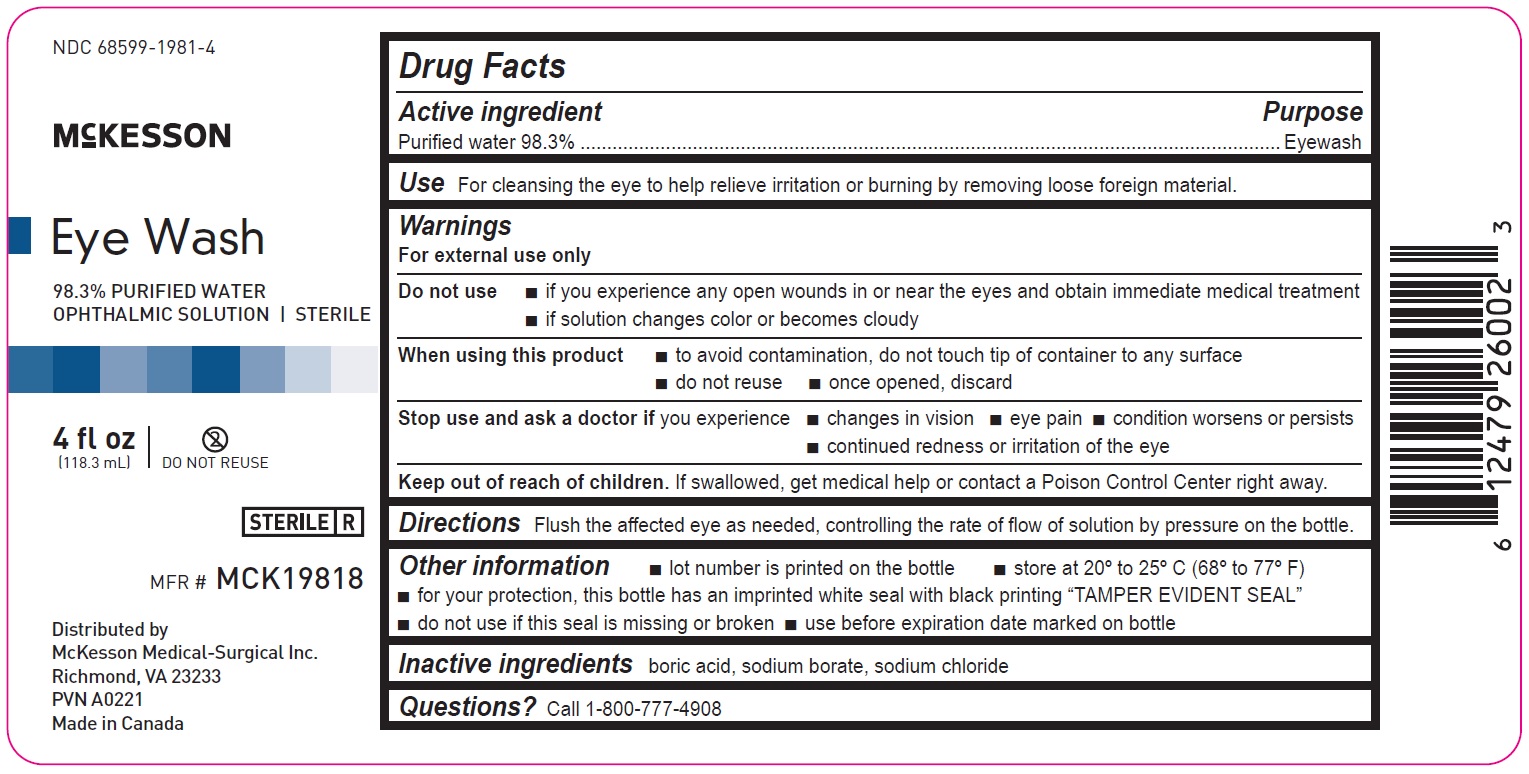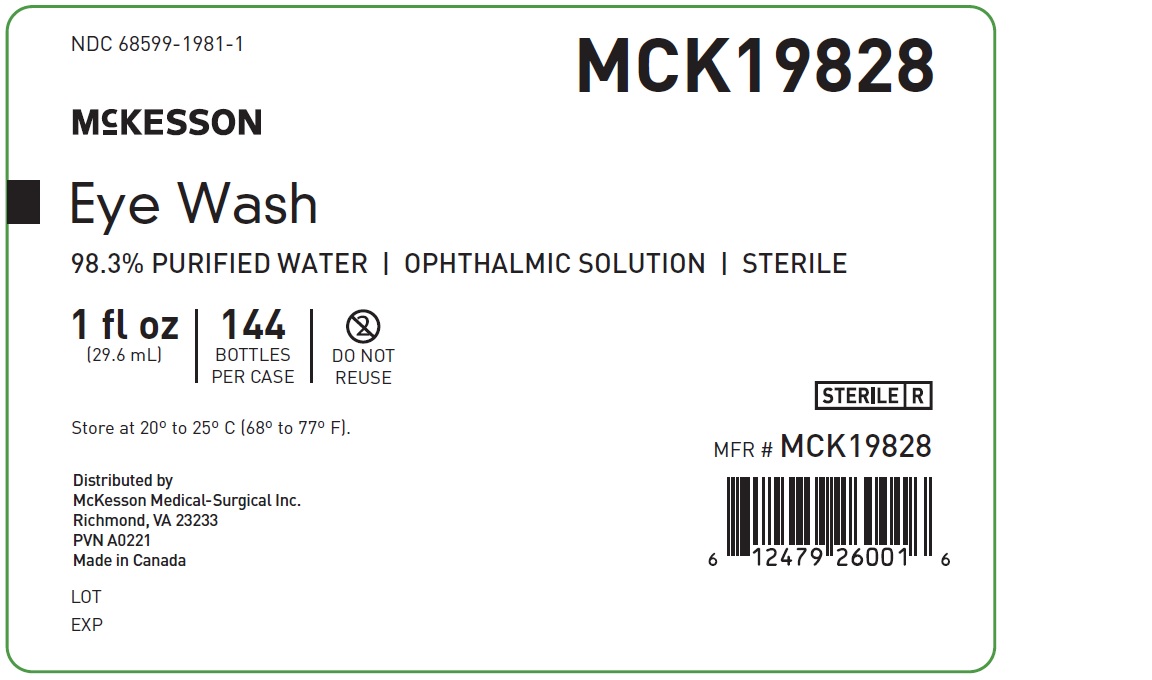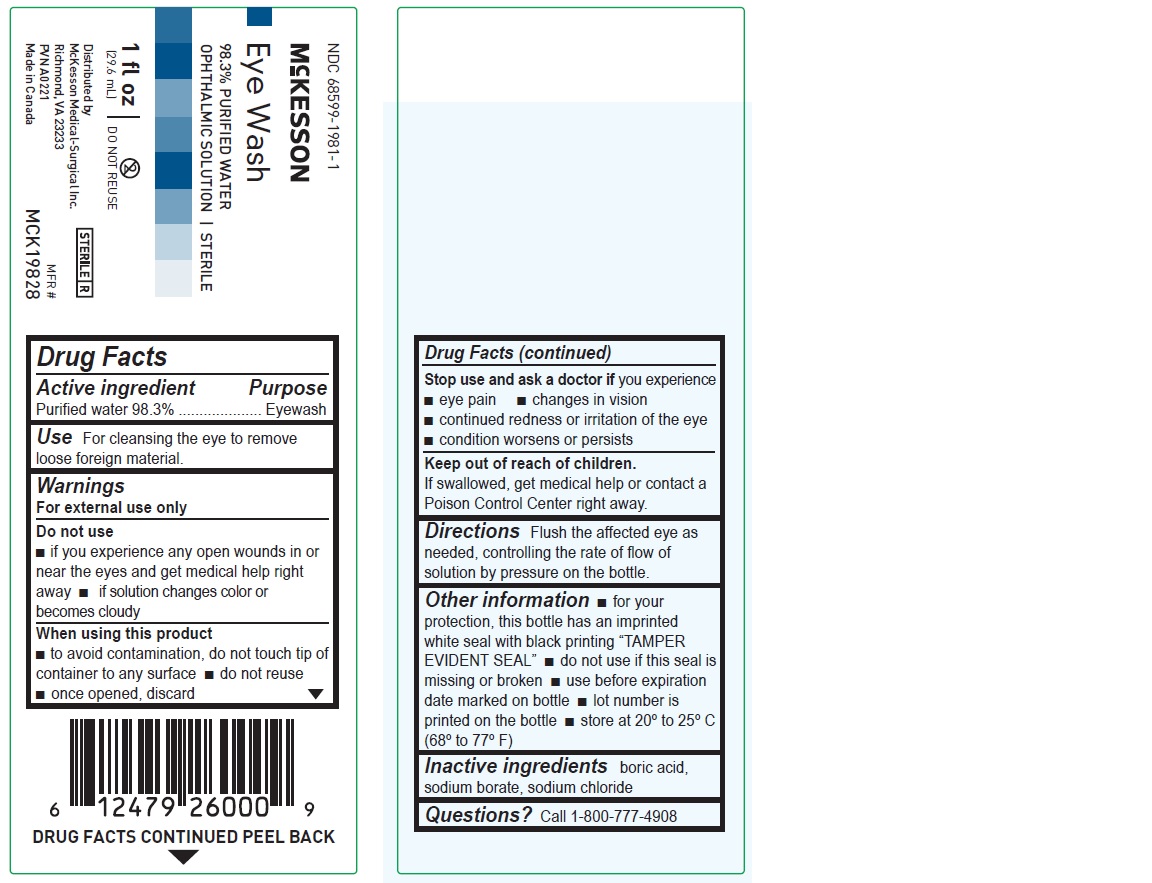 DRUG LABEL: Eye wash
NDC: 68599-1981 | Form: LIQUID
Manufacturer: McKesson
Category: otc | Type: HUMAN OTC DRUG LABEL
Date: 20221018

ACTIVE INGREDIENTS: WATER 98.3 mL/100 mL
INACTIVE INGREDIENTS: BORIC ACID; SODIUM BORATE; SODIUM CHLORIDE

Eye wash

Drug Facts

Drug Facts
Active ingredient
Purified water 98.3%

Purpose Eyewash

INDICATIONS AND USAGE

For external use only
Do not use
• if you experience any open wounds in or near the eyes and get medical help right away
• if solution changes color or becomes cloudy
When using this product
• to avoid contamination, do not touch tip of container to any surface
• do not reuse
• once opened, discard

Warnings
For external use only
Do not use
• if you experience any open wounds in or near the eyes and get medical help right away
• if solution changes color or becomes cloudy

Stop use and ask a doctor if you experience
• eye pain
• changes in vision
• continued redness or irritation of the eye
• condition worsens or persists

Keep out of reach of children.

If swallowed, get medical help or contact a Poison Control Center right away.

Directions
Flush the affected eye as needed, controlling the rate of flow of solution by pressure on the bottle.

Other information
• for your protection, this bottle has an imprinted white seal with black printing “TAMPER EVIDENT SEAL”
• do not use if this seal is missing or broken
• use before expiration date marked on bottle
• lot number is printed on the bottle
• store at 20º to 25ºC (68º to 77ºF)

Inactive ingredients
boric acid, sodium borate, sodium chloride

Questions? Call 1-800-777-4908

1 fl oz

NDC 68599-1981-1

McKesson

Eye Wash

98.3% PURIFIED WATER
OPHTHALMIC SOLUTION | STERILE

MFR# MCK19828

1 fl oz
(29.6 mL)

Distributed by
McKesson Medical-Surgical Inc.
Richmond, VA 23233
PVN A0221
Made in Canada

1 fl oz eye wash solution
Drug Facts
Active ingredient Purpose
Purified water 98.3% Eyewash
Use
For cleansing the eye to remove loose foreign material
Warnings
For external use only
Do not use
• if you experience any open wounds in or near the eyes and get medical help right away
• if solution changes color or becomes cloudy
When using this product
• to avoid contamination, do not touch tip of container to any surface
• do not reuse
• once opened, discard
Stop use and ask a doctor if you experience
• eye pain
• changes in vision
• continued redness or irritation of the eye
• condition worsens or persists
Keep out of reach of children. If swallowed, get medical help or contact a Poison Control Center right away.
Directions
Flush the affected eye as needed, controlling the rate of flow of solution by pressure on the bottle.
Other information
• for your protection, this bottle has an imprinted white seal with black printing “TAMPER EVIDENT SEAL”
• do not use if this seal is missing or broken
• use before expiration date marked on bottle
• lot number is printed on the bottle
• store at 20º to 25ºC (68º to 77ºF)
Inactive ingredients
boric acid, sodium borate, sodium chloride
Questions? Call 1-800-777-4908

4 fl oz

68599-1981-4

McKesson

Eye Wash

98.3% PURIFIED WATER
OPHTHALMIC SOLUTION | STERILE

MFR# MCK19818

4fl oz

(118.3mL)

Distributed by
McKesson Medical-Surgical Inc.
Richmond, VA 23233
PVN A0221
Made in Canada

4 fl oz eye wash solution
Drug Facts
Drug Facts
Active ingredient Purpose
Purified water 98.3% Eyewash
Use
For cleansing the eye to help relieve irritation or burning by removing loose foreign material
Warnings
For external use only
Do not use
• if you experience any open wounds in or near the eyes and obtain immediate medical treatment
• if solution changes color or becomes cloudy
When using this product
• to avoid contamination, do not touch tip of container to any surface
• do not reuse
• once opened, discard
Stop use and ask a doctor if you experience
• changes in vision
• eye pain
• condition worsens or persists
• continued redness or irritation of the eye
Keep out of reach of children. If swallowed, get medical help or contact a Poison Control Center right away.
Directions
Flush the affected eye as needed, controlling the rate of flow of solution by pressure on the bottle.
Other information
• lot number is printed on the bottle
• store at 20º to 25ºC (68º to 77ºF)
• for your protection, this bottle has an imprinted white seal with black printing “TAMPER EVIDENT SEAL”
• do not use if this seal is missing or broken
• use before expiration date marked on bottle
Inactive ingredients
boric acid, sodium borate, sodium chloride
Questions? Call 1-800-777-4908